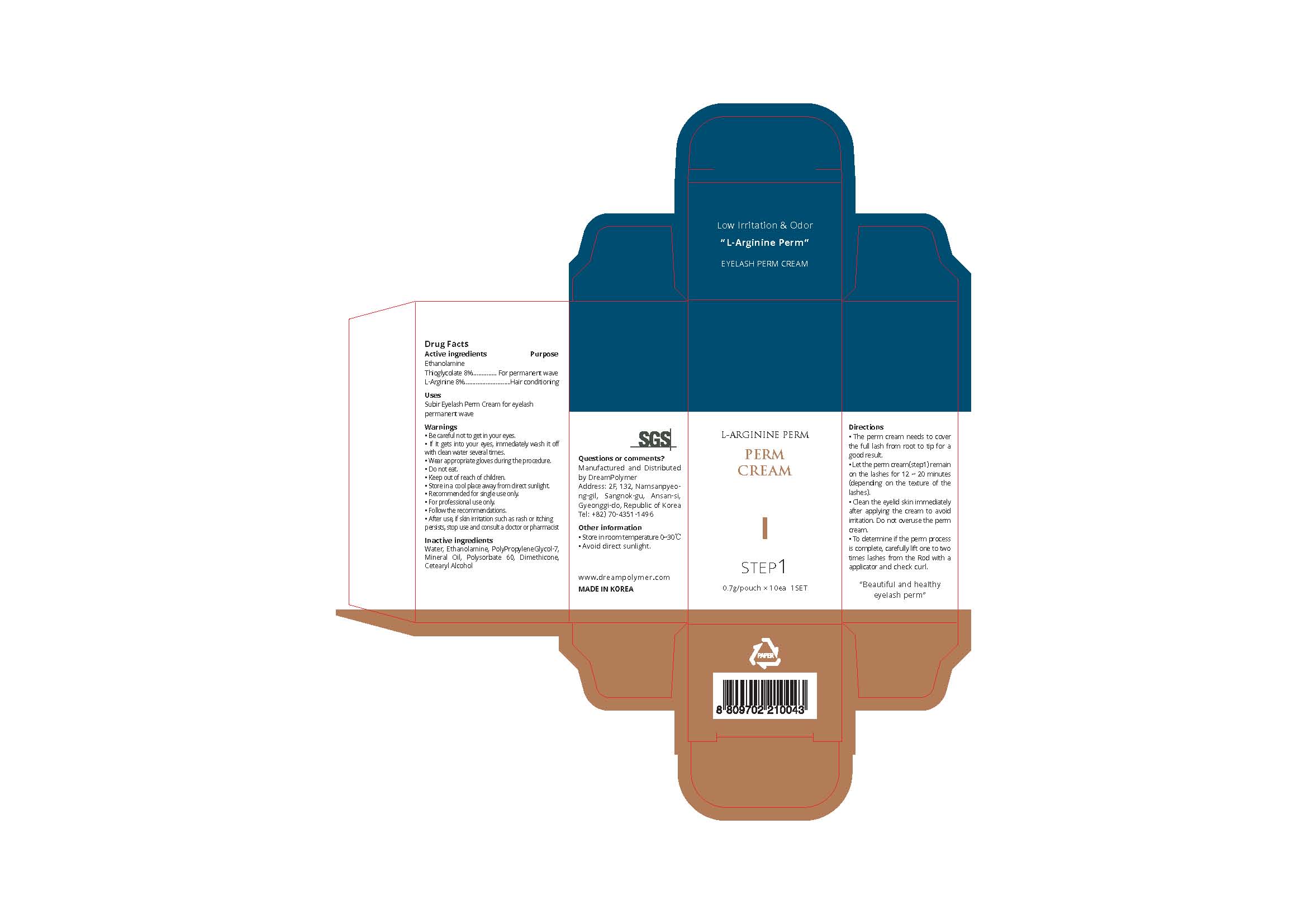 DRUG LABEL: SUBIR EYELASH
NDC: 81716-002 | Form: CREAM
Manufacturer: Dream Polymer
Category: otc | Type: HUMAN OTC DRUG LABEL
Date: 20210330

ACTIVE INGREDIENTS: ETHYL THIOGLYCOLATE 0.056 g/0.7 g; .ALPHA.N-(METHOXYCARBONYL)-L-ARGININE 0.056 g/0.7 g
INACTIVE INGREDIENTS: Water; Polysorbate 60; Dimethicone

Active Ingredient(s)

Ethanolamine Thioglycolate 8%

L-Arginine 8%

Purpose

Ethanolamine Thioglycolate - For permanent wave

L-Arginine - Hair conditioning

Use

Subir Eyelash Perm Cream for eyelash permanent wave

Warnings

• Be careful not to get in your eyes.
• If it gets into your eyes, immediately wash it off with clean water several times.
• Wear appropriate gloves during the procedure.
• Do not eat.
• Keep out of reach of children.
• Store in a cool place away from direct sunlight.
• Recommended for single use only.
• For professional use only.
• Follow the recommendations.
• After use, if skin irritation such as rash or itching persists, stop use and consult a doctor or pharmacist

 Keep out of reach of children.

Directions

• The perm cream needs to cover the full lash from root to tip for a good result.
• Let the perm cream(step1) remain on the lashes for 12 ~ 20 minutes (depending on the texture of the lashes).
• Clean the eyelid skin immediately after applying the cream to avoid irritation. Do not overuse the perm cream.
• To determine if the perm process is complete, carefully lift one to two times lashes from the Rod with a applicator and check curl.

Other information

・ Store in room temperature 0~30℃
・ Avoid direct sunlight.

Inactive ingredients

Water, Ethanolamine, PolyPropyleneGlycol-7, Mineral Oil, Polysorbate 60, Dimethicone, Cetearyl Alcohol